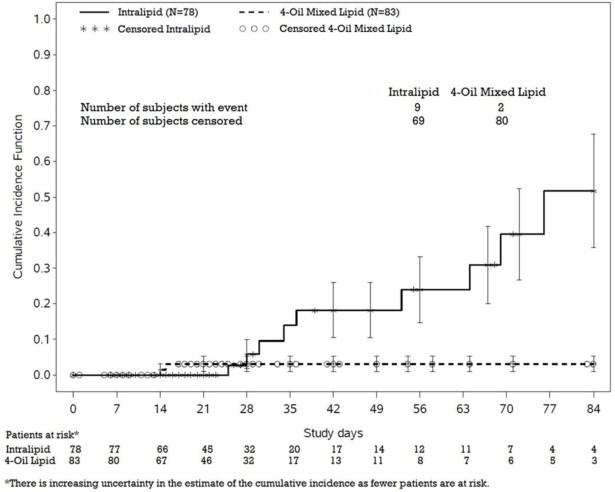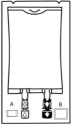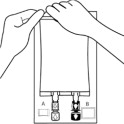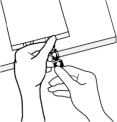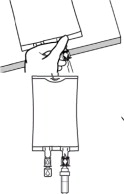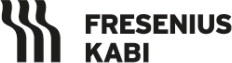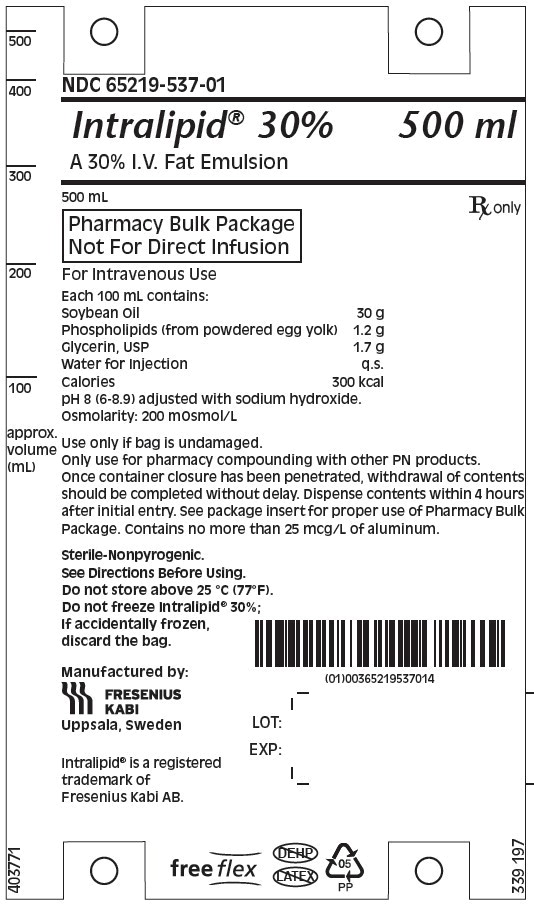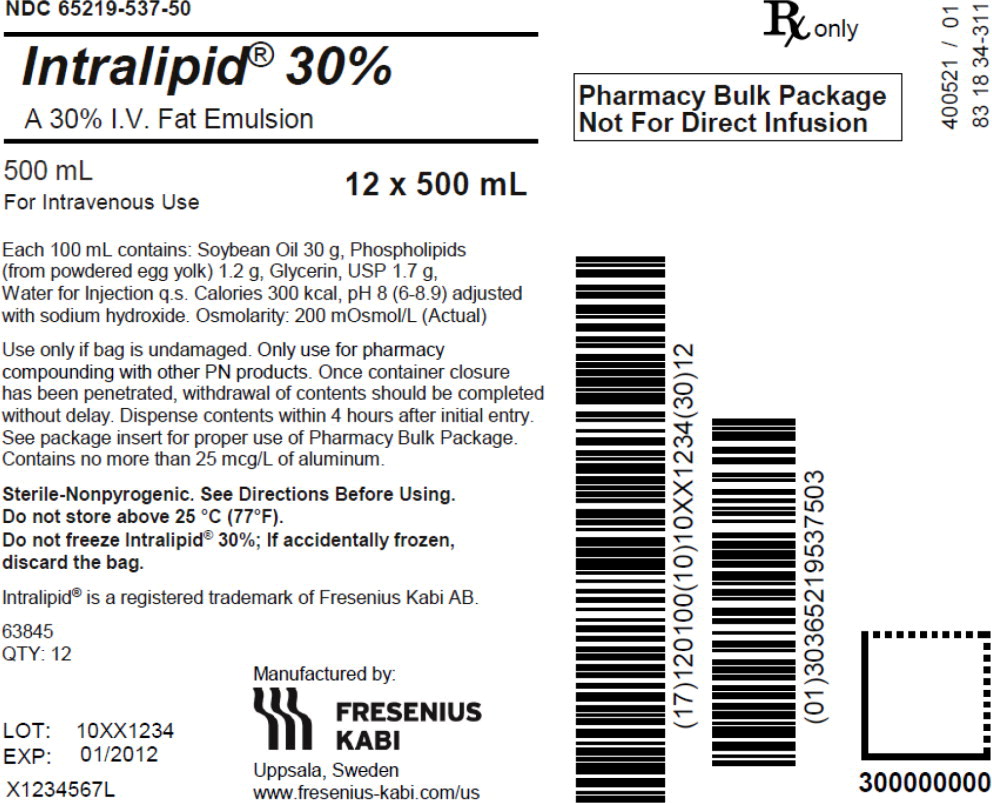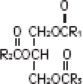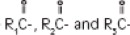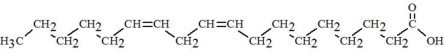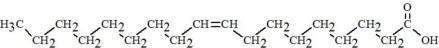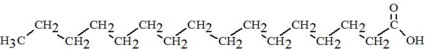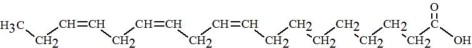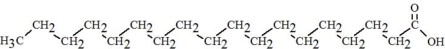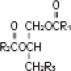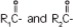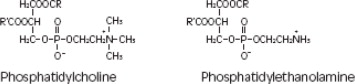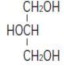 DRUG LABEL: Intralipid
NDC: 65219-537 | Form: EMULSION
Manufacturer: Fresenius Kabi USA, LLC
Category: prescription | Type: HUMAN PRESCRIPTION DRUG LABEL
Date: 20251009

ACTIVE INGREDIENTS: SOYBEAN OIL 30 g/100 mL
INACTIVE INGREDIENTS: EGG PHOSPHOLIPIDS; GLYCERIN; SODIUM HYDROXIDE; WATER

HIGHLIGHTS OF PRESCRIBING INFORMATION

These highlights do not include all the information needed to use INTRALIPID® safely and effectively. See full prescribing information for INTRALIPID.
INTRALIPID 30% (lipid injectable emulsion), for intravenous use
Initial U.S. Approval: 1993

RECENT MAJOR CHANGES

Warnings and Precautions (5.3) | 7/2025

1 INDICATIONS AND USAGE

Intralipid is indicated as a source of calories and essential fatty acids for adult and pediatric patients requiring parenteral nutrition (PN) and as a source of essential fatty acids for prevention of essential fatty acid deficiency (EFAD).

2 DOSAGE AND ADMINISTRATION

- Intralipid 30% Pharmacy Bulk Package is for admixing only and is not intended for direct intravenous infusion. (2.1)
- Admixtures containing Intralipid 30% are prepared by a healthcare provider. (2.1)
- Intralipid 30% must be combined with other PN fluids so that the resulting admixture has a final lipid concentration of no more than 20% (0.2 g lipid per mL of admixture). (2.1, 2.2)
- Protect the admixed PN solution from light. (2.2, 16)
- Recommended dosage depends on age, energy expenditure, clinical status, body weight, tolerance, ability to metabolize and eliminate lipids, and consideration of additional energy given to the patient. (2.3)

Age | Nutritional Requirements
Age | Recommended Initial Dosage and Maximum Dosage
Birth to 2 years of age (including preterm and term neonates) | Initial 0.5 g/kg/day not to exceed 3 g/kg/day
Pediatric patients 2 to <12 years of age | Initial 1 to 2 g/kg/day not to exceed 2.5 g/kg/day
Pediatric patients 12 to 17 years of age | Initial 1 g/kg/day not to exceed 2 g/kg/day
Adults | 1 g/kg/day (stable) ≤1 g/kg/day (critically ill) not to exceed 2.5 g/kg/day

3 DOSAGE FORMS AND STRENGTHS

30% Injectable Emulsion:

- 150 g/500 mL (0.3 g/mL) of lipid in Pharmacy Bulk Package (3)

4 CONTRAINDICATIONS

- Known hypersensitivity to egg, soybean, or peanut, or any of the active ingredients or excipients. (4, 5.3)
- Severe disorders of lipid metabolism characterized by hypertriglyceridemia (serum triglyceride > 1,000 mg/dL). (4, 5.7)

5 WARNINGS AND PRECAUTIONS

- Risk of Clinical Decompensation with Rapid Infusion of Intravenous Lipid Emulsion in Neonates and Infants: Acute respiratory distress, metabolic acidosis, and death after rapid infusion of intravenous lipid emulsions have been reported. When Intralipid 30% is diluted to 20%, strictly adhere to the recommended total daily dosage; the hourly infusion rate should not exceed 0.125 g/kg/hour for neonates and infants. (5.1, 8.4)
- Risk of Parenteral Nutrition-Associated Liver Disease (PNALD): Increased risk in patients who receive PN for extended periods of time, especially preterm neonates. Monitor liver function tests; if abnormalities occur consider discontinuation or dosage reduction. (5.2, 6.1, 8.4)
- Hypersensitivity Reactions: Monitor for signs or symptoms. Discontinue infusion if reactions occur. (5.3)
- Risk of Infections, Fat Overload Syndrome, Refeeding Syndrome, and Hypertriglyceridemia: Monitor for signs and symptoms; monitor laboratory parameters. (5.4, 5.5, 5.6, 5.7)
- Aluminum Toxicity: Increased risk in patients with renal impairment, including preterm neonates. (5.8, 8.4)

6 ADVERSE REACTIONS

Most common adverse drug reactions (≥5%) from clinical trials in adults were nausea, vomiting, and pyrexia. Most common adverse drug reactions (≥5%) from clinical trials in pediatric patients were anemia, vomiting, increased gamma-glutamyltransferase, and cholestasis. (6.1)

To report SUSPECTED ADVERSE REACTIONS, contact Fresenius Kabi USA, LLC at 1-800-551-7176 or FDA at 1-800-FDA-1088 or www.fda.gov/medwatch.

7 DRUG INTERACTIONS

Vitamin K Antagonists (e.g., warfarin): Anticoagulant activity may be counteracted; increase monitoring of coagulation parameters. (7)

FULL PRESCRIBING INFORMATION

1 INDICATIONS AND USAGE

Intralipid® is indicated as a source of calories and essential fatty acids for adult and pediatric patients requiring parenteral nutrition and as a source of essential fatty acids for prevention of essential fatty acid deficiency (EFAD).

2 DOSAGE AND ADMINISTRATION

2.1 Important Preparation and Administration Instructions

- Intralipid 30% Pharmacy Bulk Package is for admixing use only and is not intended for direct intravenous administration.
- Admixtures containing Intralipid 30% are prepared and administered by a healthcare provider in the inpatient setting [see Dosage and Administration (2.2)].
- Patients and caregivers may administer admixtures containing Intralipid for home use after appropriate training by a trained healthcare provider [see Patient Counseling Information (17)].
- Intralipid 30% must be combined with other PN fluids so that the resulting admixture has a final lipid concentration of no more than 20% (0.2 g lipid per mL of admixture). Refer to Admixture Preparation Instructions [see Dosage and Administration (2.2)].
- When Intralipid 30% is diluted to 20%, strictly adhere to the recommended total daily dosage; the hourly infusion rate should not exceed 0.125 g/kg/hour for neonates and infants [see Warnings and Precautions (5.1)].
- Intralipid admixtures with osmolarity
  - Greater than or equal to 900 mOsm/L must be infused through a central vein.
  - Less than 900 mOsm/L may be administered either through a central or peripheral vein.
- Use a 1.2 micron in-line filter during admixture administration.
- PN admixtures should use a dedicated infusion line without any connections. Do not connect multiple medications in series.
- To prevent air embolism, use a non-vented infusion set or close the vent on a vented set and fully evacuate residual gas in the bag prior to admixture administration.
- The flow rate of the admixture should be controlled with an infusion pump. Do not pressurize the flexible bag to increase flow rates, and if administration is controlled by a pumping device, turn off the pump before the bag runs dry.
- Do not use infusion sets and lines that contain di-2-ethylhexyl phthalate (DEHP), including infusion sets that contain polyvinyl chloride (PVC) components, because they contain DEHP as a plasticizer.
- After connecting the infusion set, start infusion of PN admixture with Intralipid immediately. Complete the infusion within 24 hours.

2.2 Admixture Preparation Instructions

Use the following instructions to prepare the Intralipid 30% Pharmacy Bulk Package for transfer to a compounding bag:

1. Inspect Bag

- Inspect the integrity indicator (Oxalert®) (A) before removing the overpouch.
- Discard the product if the indicator is black, overpouch is opened or damaged, emulsion color is not white, or seals of bag are broken.

2. Remove Overpouch

- Place the bag on a clean, flat surface.
- Tear the overpouch at notch and pull down.
- Discard the Oxalert sachet (A) and the oxygen absorber (B).
- Visually inspect the bag and contents for particulate matter and discoloration prior to administration. The lipid emulsion should be a homogenous liquid with a milky white appearance. If the mixture is not white or the emulsion has separated (noted by discoloration, phase separation, or oily droplets), or if particulates and/or leakage are observed, discard the bag.

3. Spike Bag

- Identify the infusion port (blue cap with the arrow pointing away from the bag).
- Immediately before inserting the compounding set, break off the blue infusion port cap.
- Use a suitable sterile transfer device or dispensing set with an external spike diameter of 5.5 to 5.7 mm.
- Hold the base of the infusion port.
- Insert the spike through the infusion port by rotating your wrist slightly until the spike is inserted.
- Do not pierce the infusion port more than once.

4. Transfer to the Compounding Bag

- Hang the bag using the hanger cut and start transfer to the compounding bag.
- Discard unused portion.

- Use the Intralipid 30% immediately for admixing after removal from the overpouch. If not used immediately, the product can be stored for no longer than 24 hours at 2°C to 8°C (36°F to 46°F). After removal from storage, and once the closure is penetrated, use Pharmacy Bulk Package contents within 4 hours.
- Diluting Intralipid 30% to a 10% or 20% concentration with an intravenous fluid such as normal saline or other diluent does not produce a dilution that is equivalent in composition to Intralipid 10% or 20% intravenous lipid emulsions. Therefore, diluents other than dextrose and amino acids should not be used to prepare admixtures for direct intravenous administration.

Admixing Instructions

- Prepare the admixture in PN containers using strict aseptic techniques to avoid microbial contamination.
- Do not add Intralipid 30% Pharmacy Bulk Package to the PN container first; destabilization of the lipid may occur. The prime destabilizers of emulsions are excessive acidity (such as a pH <5) and inappropriate electrolyte content. Amino acid solutions exert buffering effects that protect the emulsion from destabilization. Give careful consideration to the addition of divalent cations (Ca++ and Mg++), which have been shown to cause emulsion instability.
- Do not inject additives directly into Intralipid.
- Intralipid 30% may be mixed with amino acid and dextrose injections to produce “all-in-one” PN admixtures. The mixing sequence below must be followed for manual compounding to minimize pH-related problems by ensuring that typically acidic dextrose injections are not mixed with lipid emulsions alone; shake bags gently after each addition.
  - Transfer dextrose injection to the PN container.
  - Transfer amino acid injection.
  - Transfer Intralipid 30%.
- Simultaneous transfer of amino acid injection, dextrose injection, and Intralipid to the PN container is also permitted; follow automated compounding device instructions as indicated. Use gentle agitation during admixing to minimize localized concentration effects.
- Additions to the PN admixtures should be evaluated by a pharmacist for compatibility. Questions about compatibility may be directed to Fresenius Kabi.
- Inspect the admixture to ensure that precipitates have not formed during preparation of the admixture and the emulsion has not separated. Discard the admixture if any of the above are observed.
- Infuse admixtures containing Intralipid immediately. If not used immediately, store admixtures under refrigeration at 2°C to 8°C (36°F to 46°F) for no longer than 24 hours. Infusion must be complete within 24 hours after removal from refrigeration. Discard any remaining admixture.
- Protect the admixed PN solution from light.

2.3 Recommended Dosage and Administration

- The recommended nutritional requirements of lipid and recommended dosages of Intralipid to be administered to meet those requirements for adults and pediatric patients are provided in Table 1.
- The dosing of Intralipid depends on the patient's individual energy requirements influenced by age, body weight, tolerance, clinical status, and the ability to metabolize and eliminate lipids.
- When determining dose, energy supplied by dextrose and amino acids from PN, as well as energy from oral or enteral nutrition, has to be taken into account. Energy and lipid provided from lipid-based medications should also be taken into account (e.g., propofol).
- Prior to administration of admixtures with Intralipid, correct severe fluid and electrolyte disorders and measure serum triglyceride levels to establish a baseline value. In patients with elevated triglyceride levels, initiate Intralipid at a lower dosage and titrate in smaller increments, monitoring the triglyceride levels with each adjustment [see Warnings and Precautions (5.7)].

Table 1: Recommended Pediatric and Adult Dosage for Intralipid Concentrations of 20% or less in an Admixture
Age | Nutritional Requirements
Age | Recommended Initial Dosage and Maximum Dosage
Birth to 2 years of age (including preterm and term neonates*) [see Warnings and Precautions (5.1)] | Initial 0.5 g/kg/day not to exceed 3 g/kg/day**
Pediatric patients 2 to <12 years of age | Initial 1 to 2 g/kg/day not to exceed 2.5 g/kg/day**
Pediatric patients 12 to 17 years of age | Initial 1 g/kg/day not to exceed 2 g/kg/day**
Adults | 1 g/kg/day in stable patients ≤1 g/kg/day in critically ill patients not to exceed 2.5 g/kg/day**
* The neonatal period is defined as including term, post-term, and preterm neonates. The neonatal period for term and post-term neonates is the day of birth plus 27 days. For preterm neonates, the neonatal period is defined as the day of birth through the expected age of delivery plus 27 days (i.e., 44 weeks post-menstrual age).
** Daily dosage should also not exceed a maximum of 60% of total energy requirements [see Overdosage (10)].

Dosage Modifications in Patients with Essential Fatty Acid Deficiency

When admixtures with Intralipid are administered to correct essential fatty acid deficiency (EFAD), supply 8% to 10% of caloric input from Intralipid in order to provide adequate amounts of linoleic and linolenic acids.

3 DOSAGE FORMS AND STRENGTHS

Intralipid 30% is a sterile, homogenous, milky, white lipid injectable emulsion in Flexible Containers supplied as:

- 150 g/500 mL (0.3 g/mL) of lipid in 500 mL Pharmacy Bulk Package

4 CONTRAINDICATIONS

- Known hypersensitivity to egg, soybean, peanut, or any of the active or inactive ingredients in Intralipid [see Warnings and Precautions (5.3)]
- Severe disorders of lipid metabolism characterized by hypertriglyceridemia (serum triglyceride >1,000 mg/dL) [see Warnings and Precautions (5.7)]

5 WARNINGS AND PRECAUTIONS

5.1 Clinical Decompensation with Rapid Infusion of Intravenous Lipid Emulsions in Neonates and Infants

In the postmarketing setting, serious adverse reactions including acute respiratory distress, metabolic acidosis, and death have been reported in neonates and infants after rapid infusion of intravenous lipid emulsions. Hypertriglyceridemia was commonly reported.

Intralipid 30% Pharmacy Bulk Package is not intended for direct infusion. When it is diluted to 20%, strictly adhere to the recommended total daily dosage; the hourly infusion rate should not exceed 0.125 g/kg/hour.

Preterm and small for gestational age infants have poor clearance of intravenous lipid emulsion and increased free fatty acid plasma levels following lipid emulsion infusion.

Carefully monitor the infant's ability to eliminate the infused lipids from the circulation (e.g., measure serum triglycerides and/or plasma free fatty acid levels). If signs or poor clearance of lipids from the circulation occur, stop the infusion and initiate a medical evaluation [see Warnings and Precautions (5.5, 5.7) and Overdosage (10)].

5.2 Parenteral Nutrition-Associated Liver Disease and Other Hepatobiliary Disorders

Risk of Parenteral Nutrition-Associated Liver Disease

Parenteral nutrition-associated liver disease (PNALD), also referred to as intestinal failure- associated liver disease (IFALD), can present as cholestasis or hepatic steatosis, and may progress to steatohepatitis with fibrosis and cirrhosis (possibly leading to chronic hepatic failure). The etiology of PNALD is multifactorial; however, intravenously administered phytosterols (plant sterols) contained in plant-derived lipid emulsions, including Intralipid, have been associated with development of PNALD.

In a randomized study of neonates and infants expected to be treated with PN for at least 28 days, parenteral nutrition-associated cholestasis (PNAC), a precursor to PNALD, developed more frequently in Intralipid-treated patients than patients treated with a 4-oil mixed lipid emulsion. [see Adverse Reactions (6.1), Use in Specific Populations (8.4)].

Monitor liver tests in patients treated with admixtures containing Intralipid and consider discontinuation or dosage reduction if abnormalities occur.

Other Hepatobiliary Disorders

Hepatobiliary disorders including cholecystitis and cholelithiasis have developed in some PN-treated patients without preexisting liver disease.

Monitor liver tests when administering admixtures containing Intralipid. Patients developing signs of hepatobiliary disorders should be assessed early to determine whether these conditions are related to Intralipid use.

5.3 Hypersensitivity Reactions

Intralipid contains soybean oil and egg phospholipids, which may cause hypersensitivity reactions. Cross reactions have been observed between soybean and peanut. In postmarketing experience, anaphylaxis has been reported following Intralipid administration [see Adverse Reactions (6.2)].

Intralipid is contraindicated in patients with known hypersensitivity to egg, soybean, peanut or any of the active or inactive ingredients in Intralipid [see Contraindications (4)]. If a hypersensitivity reaction occurs, stop infusion of admixtures containing Intralipid immediately and initiate appropriate treatment and supportive measures.

5.4 Infections

Parenteral nutrition, such as Intralipid, can support microbial growth and is an independent risk factor for the development of catheter-related bloodstream infections. To decrease the risk of infectious complications, ensure aseptic techniques are used for catheter placement, catheter maintenance, and preparation and administration of admixtures containing Intralipid.

Monitor for signs and symptoms of infection including fever and chills, as well as laboratory test results that might indicate infection (including leukocytosis and hyperglycemia). Perform frequent checks of the intravenous catheter insertion site for edema, redness, and discharge.

5.5 Fat Overload Syndrome

Fat overload syndrome is a rare condition that has been reported with intravenous lipid injectable emulsions and is characterized by a sudden deterioration in the patient's condition (e.g., fever, anemia, leukopenia, thrombocytopenia, coagulation disorders, hyperlipidemia, hepatomegaly, deteriorating liver function, and central nervous system manifestations such as coma). A reduced or limited ability to metabolize lipids, accompanied by prolonged plasma clearance (resulting in higher lipid levels), may result in this syndrome. Although fat overload syndrome has been most frequently observed when the recommended lipid dose or infusion rate was exceeded, cases have also been described when the lipid formulation was administered according to instructions.

If signs or symptoms of fat overload syndrome occur, stop the infusion of admixtures containing Intralipid. The syndrome is usually reversible when the infusion of the lipid emulsion is stopped.

5.6 Refeeding Syndrome

Administering PN to severely malnourished patients may result in refeeding syndrome, which is characterized by the intracellular shift of potassium, phosphorus, and magnesium as patients become anabolic. Thiamine deficiency and fluid retention may also develop. To prevent these complications, closely monitor severely malnourished patients and slowly increase their nutrient intake.

5.7 Hypertriglyceridemia

The use of Intralipid is contraindicated in patients with hypertriglyceridemia with serum triglyceride concentrations >1,000 mg/dL.

Patients with conditions such as inherited lipid disorders, obesity, diabetes mellitus, or metabolic syndromes have a higher risk of developing hypertriglyceridemia with the use of Intralipid. In addition, patients with hypertriglyceridemia may have worsening of their hypertriglyceridemia with administration of Intralipid. Excessive dextrose administration may further increase such risk.

Evaluate patients' capacity to metabolize and eliminate the infused lipid emulsion by measuring serum triglycerides before the start of infusion (baseline value) and regularly throughout treatment. If triglyceride levels are above 400 mg/dL in adults, stop the Intralipid infusion and monitor serum triglyceride levels to avoid clinical consequences of hypertriglyceridemia such as pancreatitis. In pediatric patients with hypertriglyceridemia, lower triglyceride levels (i.e., below 400 mg/dL) may be associated with adverse reactions. Monitor serum triglyceride levels to avoid potential complications with hypertriglyceridemia such as pancreatitis, lipid pneumonitis, and neurologic changes, including kernicterus.

To minimize the risk of new or worsening of hypertriglyceridemia, assess high-risk patients for their overall energy intake including other sources of lipids and dextrose, as well as concomitant drugs that may affect lipid and dextrose metabolism.

5.8 Aluminum Toxicity

Intralipid contains no more than 25 mcg/L of aluminum. Prolonged PN administration in patients with renal impairment may result in aluminum reaching toxic levels. Preterm neonates are at greater risk because their kidneys are immature, and they require large amounts of calcium and phosphate solutions that contain aluminum.

Patients with impaired kidney function, including preterm neonates, who receive parenteral levels of aluminum at greater than 4 to 5 mcg/kg/day can accumulate aluminum at levels associated with central nervous system and bone toxicity. Tissue loading in these patients may occur at even lower rates of administration.

5.9 Monitoring/Laboratory Tests

Monitor fluid status closely in patients with pulmonary edema or heart failure.

Throughout treatment, monitor serum triglycerides [see Warnings and Precautions (5.7)], essential fatty acids, fluid and electrolyte status, serum osmolarity, blood glucose, liver and kidney function, blood count (including platelets), and coagulation parameters.

The lipids contained in Intralipid may interfere with some laboratory tests (e.g., hemoglobin, lactate dehydrogenase, bilirubin, oxygen saturation) if blood is sampled before lipids have cleared from the bloodstream. Conduct these tests at least 6 hours after stopping the infusion.

Intralipid contains vitamin K that may counteract anticoagulant activity [see Drug Interactions (7)].

6 ADVERSE REACTIONS

Adverse reactions described elsewhere in this Prescribing Information are:

- Clinical Decompensation with Rapid Infusion of Intravenous Lipid Emulsion in Neonates and Infants [see Warnings and Precautions (5.1)]
- Parenteral Nutrition-Associated Liver Disease and Other Hepatobiliary Disorders [see Warnings and Precautions (5.2)]
- Hypersensitivity Reactions [see Warnings and Precautions (5.3)]
- Infections [see Warnings and Precautions (5.4)]
- Fat Overload Syndrome [see Warnings and Precautions (5.5)]
- Refeeding Syndrome [see Warnings and Precautions (5.6)]
- Hypertriglyceridemia [see Warnings and Precautions (5.7)]
- Aluminum Toxicity [see Warnings and Precautions (5.8)]

6.1 Clinical Trials Experience

Because clinical trials are conducted under widely varying conditions, adverse reaction rates observed in the clinical trials of a drug cannot be compared to rates in the clinical trials of another drug and may not reflect the rates observed in clinical practice.

Intralipid 20% or equivalent soybean oil lipid emulsions functioned as the comparator in trials of the 4-oil mixed lipid emulsion [see Clinical Studies (14)]. The adverse reactions from these studies are included to present the clinical experience with Intralipid because Intralipid 30% is to be diluted down to 20% or lower for PN admixture.

The safety database for Intralipid or equivalent soybean oil lipid emulsion exposure in these studies include 393 patients (230 adults; 163 pediatric) in 9 clinical trials. Adult patients were exposed for 5 days to 4 weeks in 5 clinical trials. Intralipid or equivalent soybean oil lipid emulsion was used as a component of PN which also included dextrose, amino acids, vitamins, and trace elements. Two of the 5 studies in adults were performed with Intralipid as a component of PN delivered in a 3-chamber bag.

Table 2: Adverse Reactions in >1% of Adult Patients Treated with Intralipid/Soybean Oil Emulsion
Adverse Reaction | Number of Patients in Soybean Oil Lipid Emulsion Group (N=230) | Number of Patients in 4-Oil Mixed Lipid Emulsion Comparator Group (N=229)
Nausea | 26 (11%) | 20 (9%)
Vomiting | 12 (5%) | 15 (7%)
Pyrexia | 11 (5%) | 9 (4%)
Hypertension | 9 (4%) | 6 (3%)
Headache | 7 (3%) | 3 (1%)
Hyperglycemia | 5 (2%) | 12 (5%)
Abdominal pain | 5 (2%) | 8 (4%)
Flatulence | 4 (2%) | 10 (4%)
Blood triglycerides increased | 4 (2%) | 6 (3%)
Sepsis | 4 (2%) | 5 (2%)
Diarrhea | 4 (2%) | 3 (1%)
Pneumonia | 4 (2%) | 3 (1%)
Pruritus | 4 (2%) | 3 (1%)
Gamma-glutamyltransferase increased | 4 (2%) | 2 (1%)

Less common adverse reactions occurring in ≤1% of adult patients who received Intralipid or equivalent soybean oil lipid emulsion were dyspepsia, urinary tract infection, anemia, infection, dyspnea, cholestasis, dysgeusia, increased blood alkaline phosphatase, tachycardia, liver function test abnormalities, dizziness, rash, and thrombophlebitis.

The 163 patients treated with Intralipid in four pediatric trials consisted of 147 patients <28 days of age, 9 patients 28 days to <2 years of age, and 7 patients 2 to 7 years of age; the duration of exposure was 7 to 84 days. Fifty-six percent of the pediatric patients were female, and 85% were Caucasian. Most pediatric patients were preterm neonates with feeding intolerance or other conditions requiring short-term (<29 days) PN.

Table 3: Adverse Reactions in >1% of Pediatric Patients Treated with Intralipid
Adverse Reaction | Number of Patients in Intralipid Group (N=163) | Number of Patients in 4-Oil Mixed Lipid Emulsion Comparator Group (N=170)
Anemia | 33 (20%) | 30 (18%)
Vomiting | 16 (10%) | 16 (9%)
Gamma-glutamyltransferase increased | 12 (7%) | 10 (6%)
Cholestasis | 10 (6%) | 7 (4%)
Pyrexia | 7 (4%) | 7 (4%)
C-reactive protein increased | 7 (4%) | 6 (4%)
Hyperbilirubinemia | 7 (4%) | 5 (3%)
Bilirubin conjugated increased | 7 (4%) | 3 (2%)
Nosocomial infection | 6 (4%) | 10 (6%)
Blood alkaline phosphatase increased | 6 (4%) | 1 (1%)
Abdominal pain | 5 (3%) | 4 (2%)
Hematocrit decreased | 5 (3%) | 2 (1%)
Metabolic acidosis | 5 (3%) | 2 (1%)
Diarrhea | 4 (3%) | 3 (2%)
Tachycardia | 4 (3%) | 3 (2%)
Thrombocytopenia | 4 (3%) | 3 (2%)
Alanine aminotransferase increased | 3 (2%) | 1 (1%)
Aspartate aminotransferase increased | 3 (2%) | 0 (0%)
Parenteral nutrition-associated liver disease | 3 (2%) | 0 (0%)

Less common adverse reactions occurring in ≤1% of pediatric patients who received Intralipid were hyperglycemia, sepsis, increased blood triglycerides, infection, fluid overload, hypertension, hypertriglyceridemia, rash, and hyperlipidemia.

In a randomized active-controlled, double-blind, parallel-group, multi-center study that included 152 neonates and 9 patients ranging in age from 29 to 153 days who were expected to require PN for at least 28 days, PNAC, a precursor to PNALD, developed more frequently in Intralipid-treated patients than in patients treated with a comparator 4-oil mixed lipid emulsion.

PNAC (defined as direct bilirubin >2 mg/dL with a second confirmed elevation >2 mg/dL at least 7 days later) occurred in 11.5% (9/78) in Intralipid-treated patients and 2.4% (2/83) of patients treated with a 4-oil mixed lipid emulsion. Most PNAC events occurred in patients who were treated for longer than 28 days.

The estimated cumulative incidence of PNAC is shown in the Kaplan-Meier cumulative incidence curve in Figure 1 [see Pediatric Clinical Studies (14.2)].

Figure 1: Cumulative Incidence Curve of Time to Parenteral Nutrition-Associated Cholestasis (PNAC) with Standard Error Bars

6.2 Postmarketing Experience

The following adverse reactions from voluntary reports have been reported with Intralipid. Because many of these reactions were reported voluntarily from a population of uncertain size, it is not always possible to reliably estimate their frequency or establish a causal relationship to drug exposure.

Cardiac disorders: palpitations
Gastrointestinal disorders: vomiting, nausea
General disorders and administration site conditions: chills, chest discomfort, pyrexia
Nervous system disorders: dizziness
Respiratory, thoracic, and mediastinal disorders: dyspnea
Immune system disorders: hypersensitivity reactions, including anaphylaxis [see Contraindications (4), Warnings and Precautions (5.3)]
Vascular disorders: phlebitis
Blood and lymphatic system disorders: hypercoagulability

7 DRUG INTERACTIONS

Soybean oil in Intralipid contains vitamin K1 which may counteract the anticoagulant activity of vitamin K antagonists such as warfarin. In patients who receive concomitant Intralipid and warfarin, increase monitoring of laboratory parameters for anticoagulant activity.

8 USE IN SPECIFIC POPULATIONS

8.1 Pregnancy

Risk Summary

Administration of the recommended dose of Intralipid is not expected to cause major birth defects, miscarriage, or other adverse maternal or fetal outcomes. No animal reproduction studies have been conducted with Intralipid. There are risks to the fetus associated with severe malnutrition during pregnancy (see Clinical Considerations).

The background risk of major birth defects and miscarriage for the indicated population(s) is unknown. All pregnancies have a background risk of birth defect, loss, or other adverse outcomes. In the U.S. general population, the estimated background risk of major birth defects and miscarriage in clinically recognized pregnancies is 2% to 4% and 15% to 20%, respectively.

Clinical Considerations

Disease-Associated Maternal and/or Embryo-Fetal Risk

Severe malnutrition in pregnant women is associated with preterm delivery, low birth weight, intrauterine growth restriction, congenital malformations, and perinatal mortality. Parenteral nutrition should be considered if the pregnant woman's nutritional requirements cannot be fulfilled by oral or enteral intake.

8.2 Lactation

Risk Summary

Administration of the recommended dose of Intralipid is not expected to cause harm to a breastfed infant. There are no data on the presence of Intralipid in human or animal milk or its effects on milk production. Available published literature includes fewer than five reported cases of breastfed infants exposed to various lipid emulsions via lactation, and these cases did not report adverse events. The developmental and health benefits of breastfeeding should be considered along with the mother's clinical need for Intralipid and any potential adverse effects of Intralipid on the breastfed infant, or from the underlying maternal condition.

8.4 Pediatric Use

Intralipid is contraindicated in pediatric patients with severe disorders of lipid metabolism [(see Contraindications (4)].

The safety and effectiveness of Intralipid have been established as a source of calories and essential fatty acids for PN in pediatric patients, including term and preterm neonates. Use of Intralipid in neonates is supported by evidence from short-term (i.e., 1- to 4- week) studies, and one study following neonates beyond 4 weeks [see Clinical Studies (14.2)]. Use of Intralipid in older pediatric patients is supported by evidence from short-term (i.e., <28 days) studies in pediatric patients 28 days to 12 years of age and additional evidence from studies in adults [see Clinical Studies (14)]. The most common adverse reactions in Intralipid-treated pediatric patients were anemia, vomiting, gamma-glutamyltransferase increased, and cholestasis. PNAC, a precursor to PNALD, developed more frequently in Intralipid-treated patients than in patients treated with a comparator 4-oil mixed lipid emulsion [see Warnings and Precautions (5.1) and Adverse Reactions (6.1)].

In the postmarketing setting, clinical decompensation with rapid infusion of intravenous lipid emulsion in neonates and infants, sometimes fatal, has been reported [see Warnings and Precautions (5.1)]. Because of immature renal function, preterm neonates receiving prolonged treatment with Intralipid may be at risk for aluminum toxicity [see Warnings and Precautions (5.8)].

8.5 Geriatric Use

Reported clinical experience has not identified differences in responses between the elderly and younger patients. In general, dose selection for an elderly patient should be cautious, usually starting at the low end of the dosing range, reflecting the greater frequency of decreased hepatic, renal, or cardiac function, and of concomitant disease or drug therapy.

10 OVERDOSAGE

In the event of an overdose, serious adverse reactions may result [see Warnings and Precautions (5.1, 5.5)]. Stop the infusion of admixtures containing Intralipid until triglyceride levels have normalized and symptoms have abated. The effects are usually reversible by stopping the lipid infusion. If medically appropriate, further intervention may be indicated. Lipids are not dialyzable from plasma.

11 DESCRIPTION

Intralipid is a sterile, non-pyrogenic, white, homogenous lipid emulsion for intravenous infusion as a source of calories and essential fatty acids for use in a pharmacy admixture program. The lipid content of Intralipid 30% Pharmacy Bulk Package is 0.3 g/mL and comprises soybean oil. The phosphate content is 15 mmol/L.

The total energy content, including fat, phospholipids, and glycerin is 3,000 kcal/L.

Each 100 mL of Intralipid contains approximately 30 g soybean oil, 1.2 g egg yolk phospholipids, 1.7 g glycerin, water for injection, and sodium hydroxide for pH adjustment (pH 6 to 8.9). Intralipid has an osmolality of approximately 310 mOsm/kg water (which represents an osmolarity of 200 mOsm/L).

The soybean oil is a refined natural product consisting of a mixture of neutral triglycerides of predominantly unsaturated fatty acids with the following structure:

where are saturated and unsaturated fatty acid residues.

The major component fatty acids in Intralipid are linoleic acid (44% to 62%), oleic acid (19% to 30%), palmitic acid (7% to 14%), alpha-linolenic acid (4% to 11%), and stearic acid (1.4% to 5.5%). These fatty acids have the following chemical and structural formulas:

Linoleic Acid
C18H32O2

Oleic Acid
C18H34O2

Palmitic Acid
C16H32O2

α-Linolenic Acid
C18H30O2

Stearic Acid
C18H36O2

Purified egg phosphatides are a mixture of naturally occurring phospholipids which are isolated from the egg yolk. These phospholipids have the following general structure:

contain saturated and unsaturated fatty acids that abound in neutral fats. R3 is primarily either the choline or ethanolamine ester of phosphoric acid.

Glycerin is chemically designated C3H8O3 and is a clear colorless, hygroscopic syrupy liquid. It has the following structural formula:

The container-solution unit is a closed system and is not dependent upon entry of external air during administration. The container is overwrapped to provide protection from the physical environment and to provide an additional oxygen and moisture barrier when necessary.

Intralipid contains no more than 25 mcg/L of aluminum.

The container is not made with natural rubber latex, PVC, or DEHP.

12 CLINICAL PHARMACOLOGY

12.1 Mechanism of Action

Intralipid provides a biologically utilizable source of calories and essential fatty acids.

Fatty acids serve as an important substrate for energy production. The most common mechanism of action for energy production derived from fatty acid metabolism is beta oxidation. Fatty acids are also important for membrane structure and function, as precursors for bioactive molecules (such as prostaglandins), and as regulators of gene expression.

12.2 Pharmacodynamics

The pharmacodynamic effects of Intralipid have not been fully characterized.

12.3 Pharmacokinetics

Intralipid provides fatty acids in the form of triglycerides which are hydrolyzed by lipoprotein lipase to release free fatty acids. Linoleic acid and alpha-linolenic acid are metabolized within a common biochemical pathway through a series of desaturation and elongation steps.

13 NONCLINICAL TOXICOLOGY

13.1 Carcinogenesis, Mutagenesis, Impairment of Fertility

Carcinogenicity, genetic toxicology, and animal fertility studies have not been performed with Intralipid.

14 CLINICAL STUDIES

Intralipid 20% or equivalent soybean oil lipid emulsion functioned as the comparator for the 4-oil mixed lipid emulsion in the clinical studies described in sections 14.1 and 14.2. The trial results are included to present the clinical experience with Intralipid because Intralipid 30% is to be diluted down to 20% or lower for PN admixture.

14.1 Adult Clinical Studies

The efficacy of Intralipid or equivalent soybean oil lipid emulsion compared to a 4-oil mixed lipid emulsion was evaluated in 3 clinical studies in adult patients. Nutritional efficacy in adult studies was assessed by changes in anthropometric indices (body weight, height, and body mass index [BMI]), changes in lipid and protein metabolism (albumin), and fatty acid parameters. Of the 354 adult patients (178 Intralipid; 176 comparator), 62% were male, 99% were Caucasian, and ages ranged from 19 to 96 years. All patients received Intralipid/equivalent soybean oil lipid emulsion or the comparator as part of a PN regimen. Although Adult Study 1, Adult Study 2, and Adult Study 3 were not designed for formal statistical comparisons between Intralipid/equivalent soybean oil lipid emulsion and the comparator, they support Intralipid as a source of calories and essential fatty acids in adults. The lipid dosage was variable in these studies and adjusted to the patient's nutritional requirements.

Adult Study 1 was a double-blind, randomized, active-controlled, parallel-group, multicenter study in patients who required PN for at least 28 days. Seventy-five patients were enrolled, and 73 patients were treated with either Intralipid or the comparator. Changes in mean triglyceride levels from baseline values to Week 4 were similar in both the Intralipid and comparator groups. Mean albumin levels demonstrated a comparable decrease in both groups. Mean changes in body weight (kg) and BMI (kg/m^2) were similar in both the Intralipid and the comparator groups.

Adult Study 2 was a phase 3, randomized, double-blind, active-controlled, multicenter study. A total of 249 postoperative adult patients were randomized to receive either an equivalent soybean oil lipid emulsion to Intralipid or the comparator for at least 5 days as part of their total parenteral nutrition (TPN) regimen. From baseline to Day 6, mean triglyceride levels increased similarly in both the soybean oil lipid emulsion and the comparator groups.

Adult Study 3 was a double-blind randomized, active-controlled, parallel-group, single-center study in 32 adult patients who required TPN for 10 to 14 days. Patients were treated with either an equivalent soybean oil lipid emulsion to Intralipid or the comparator. The increase in mean triglyceride levels from baseline to the final assessment was similar in both the soybean oil lipid emulsion and the comparator groups.

14.2 Pediatric Clinical Studies

The efficacy of Intralipid compared to a 4-oil mixed lipid emulsion in pediatric patients of all age groups, including term and preterm neonates, was evaluated in 333 patients in 4 randomized active-controlled, double-blind, parallel-group controlled clinical studies. Although Pediatric Studies 1, 2, 3, and 4 were not designed for formal statistical comparisons between Intralipid and the comparator, they support Intralipid as a source of calories and essential fatty acids in pediatric patients. The 333 pediatric patients (163 Intralipid; 170 comparator) consisted of 296 patients who were <28 days old, 22 patients 29 days to <2 years old, and 15 patients 2 to <12 years old. Fifty percent of the pediatric patients were male and 87% were Caucasian. All patients received Intralipid or the comparator as part of a PN regimen. Nutritional efficacy in neonates was assessed by changes in anthropometric indices (body weight, height, head circumference). Nutritional efficacy in pediatric patients, 28 days to 12 years of age, was assessed by changes in triglyceride concentrations and fatty acid parameters.

Pediatric Study 1 enrolled 152 preterm and term neonates (birth up to 28 days) and 9 patients ranging in age from 29 to 153 days. Patients were treated with either Intralipid (n=78) or the comparator (n=83). A total of 119 patients (58 Intralipid; 61 comparator) received study treatment for ≥14 days. A total of 27 patients received Intralipid for ≥29 days; 5 patients received Intralipid for the maximum study duration of 78-84 days.

Pediatric Studies 2 and 3 enrolled 60 and 84 preterm neonates, respectively, who were treated with either Intralipid or the comparator (72 neonates in each group). The median treatment duration for Intralipid group was 9 days in Pediatric Study 2 and 6 days in Pediatric Study 3.

Pediatric Study 4 enrolled 28 patients 5 months to <2 years of age and 15 patients 2 to 11.5 years of age. Patients were treated with either Intralipid (n=13) or the comparator (n=15) with a median treatment duration of 27 days.

In Pediatric Studies 1, 2 and 3, which enrolled neonates, Intralipid-treated patients showed increases in the median body weight, height/length, and head circumference (which was measured in Studies 1 and 3) comparable to the comparator-treated patients. Mean triglyceride levels from baseline to the final assessment in Pediatric Studies 1, 2, and 3 were variable in these neonates, but overall differences between groups were not considered clinically relevant. Mean triglyceride levels in Pediatric Study 4 were variable but remained within the normal range.

16 HOW SUPPLIED/STORAGE AND HANDLING

Intralipid 30% (lipid injectable emulsion, USP) is a sterile, homogeneous, milky, white lipid emulsion, supplied as Pharmacy Bulk Package in Flexible Containers.

Product Code | Each | Unit of Sale
831834311 | NDC 65219-537-01 500 mL Pharmacy Bulk Package Bag | NDC 65219-537-50 Package of 12

Store below 25°C (77°F). Avoid excessive heat. Do not freeze. If accidentally frozen, discard container. Store in the overpouch until ready for use.

Use the Pharmacy Bulk Package immediately for admixing after removal from the overpouch. If not used immediately for admixing, the product should be stored for no longer than 24 hours at 2°C to 8°C (36°F to 46°F). After removal from storage, and once the closure is penetrated, use Pharmacy Bulk Package contents within 4 hours [see Dosage and Administration (2.2)].

Admixtures

Infuse admixtures containing Intralipid immediately. If admixtures are not used immediately, admixtures should be stored at 2°C to 8°C (36°F to 46°F) for no longer than 24 hours. After removal from storage, infuse within 24 hours [see Dosage and Administration (2.2)].

Protect the admixed PN solution from light [see Dosage and Administration (2.2)].

17 PATIENT COUNSELING INFORMATION

When initiating administration of admixtures with Intralipid, discuss the following information with the patient or caregiver:

Clinical Decompensation with Rapid Infusion of Intravenous Lipid Emulsion in Neonates and Infants

Inform caregivers that acute respiratory distress and death may occur in neonates and infants after rapid infusion of intravenous lipid emulsions. If Intralipid is infused at home, instruct caregivers not to exceed the maximum infusion rate [see Warnings and Precautions (5.1)].

Parenteral Nutrition-Associated Liver Disease and Other Hepatobiliary Disorders

Inform patients and caregivers that use of parenteral nutrition may result in parenteral nutrition- associated liver disease and/or other hepatobiliary disorders [see Warnings and Precautions (5.2)].

Hypersensitivity Reactions

Inform patients and caregivers that Intralipid may cause hypersensitivity reactions, including anaphylaxis. If admixtures containing Intralipid are infused at home, instruct patients or caregivers to stop the infusion of admixtures containing Intralipid immediately and seek medical attention if they experience signs or symptoms of a hypersensitivity reaction, such as rapid or weak heartbeat, feeling faint, difficulty in breathing or swallowing, vomiting, nausea, headache, sweating, dizziness, hives, rash, itching, flushing, dizziness, fever, or chills [see Warnings and Precautions (5.3)].

Infections

Inform patients and caregivers that patients who receive admixtures containing Intralipid are at risk of infection. If admixtures containing Intralipid are infused at home, instruct patients or caregivers to ensure aseptic techniques are used for the preparation and administration of admixtures containing Intralipid and to monitor for signs and symptoms of infection [see Warnings and Precautions (5.4)].

Fat Overload Syndrome

Inform patients and caregivers that fat overload syndrome has been reported with the use of intravenous lipid emulsions. If admixtures containing Intralipid are infused at home, instruct patients or caregivers to stop the infusion of admixtures containing Intralipid if signs or symptoms of fat overload syndrome occur [see Warnings and Precautions (5.5)].

Refeeding Syndrome

If the patient is severely malnourished, inform patients and caregivers that administering parenteral nutrition including Intralipid may result in refeeding syndrome [see Warnings and Precautions (5.6)].

Hypertriglyceridemia

Inform patients and their caregivers about the risks of hypertriglyceridemia with Intralipid use [see Warnings and Precautions (5.7)].

Aluminum Toxicity

Inform patients and their caregivers that prolonged PN administration in patients with renal impairment, including preterm neonates, may result in aluminum reaching toxic levels associated with central nervous system and bone toxicity [see Warnings and Precautions (5.8)].

Preparation and Administration Instructions

If it is acceptable for a patient or caregiver to administer admixtures containing Intralipid at home, then provide recommendations on how to inspect and prepare, add compatible additives (when appropriate), administer, and store admixtures containing Intralipid [see Dosage and Administration (2.1, 2.2)]. Inform patients or caregivers not to deviate from the administration instructions given by the healthcare provider.

Manufactured by:

Uppsala, Sweden
Intralipid is a registered trademark of Fresenius Kabi AB.
www.fresenius-kabi.com/us
451715D

PACKAGE LABEL

PACKAGE LABEL - PRINCIPAL DISPLAY - Intralipid 500 mL Bag Label

NDC 65219-537-01

Intrapilid® 30% 500 ml

A 30% I.V. Fat Emulsion

500 mL

Pharmacy Bulk Package

Not For Direct Infusion

For Intravenous Use
Rx only

PACKAGE LABEL

PACKAGE LABEL – PRINCIPAL DISPLAY – Intralipid 500 mL Shipper Label

NDC 65219-537-50

Intralipid® 30%

A 30% I.V. Fat Emulsion

Pharmacy Bulk Package

Not For Direct Infusion

500 mL

For Intravenous Use

12 x 500 mL